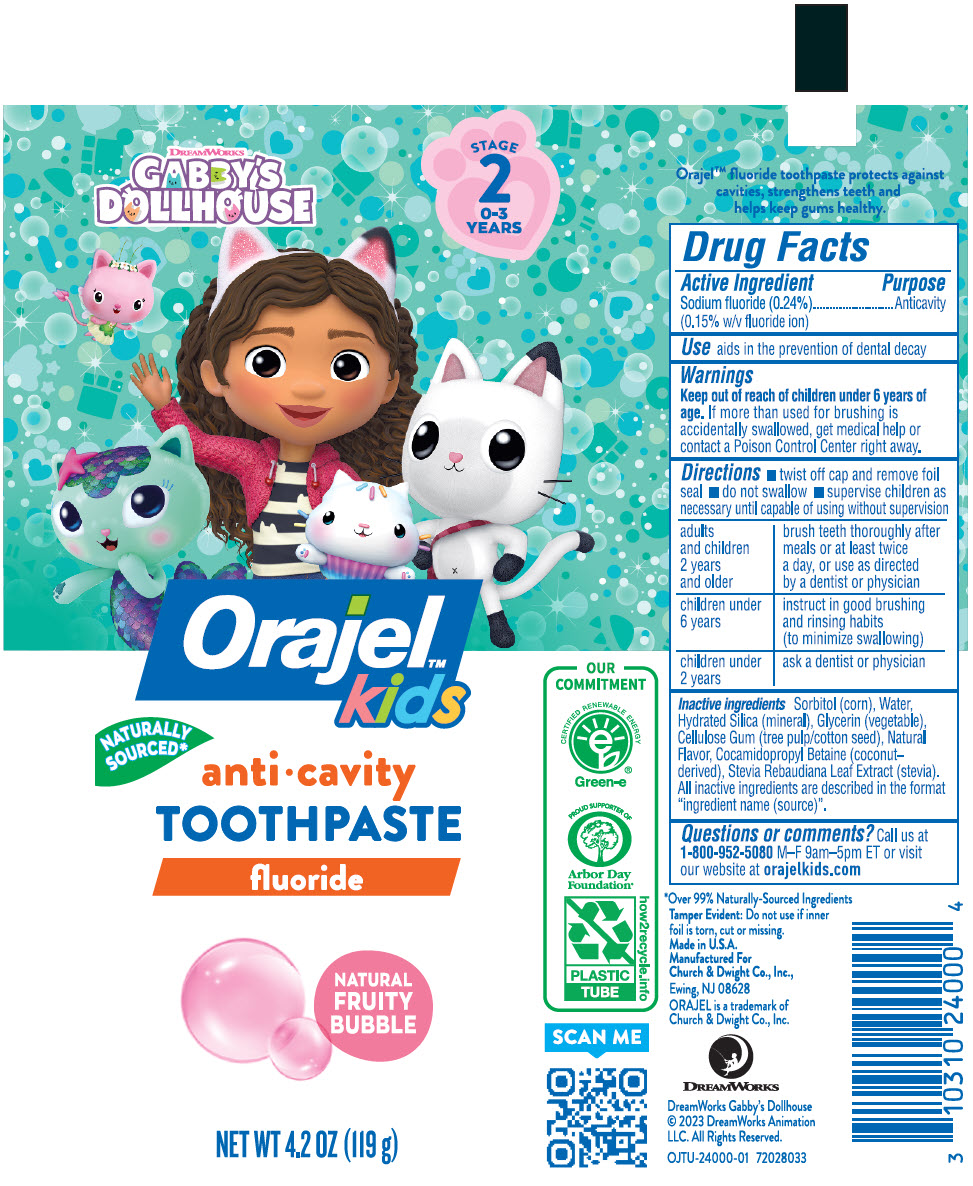 DRUG LABEL: Orajel Gabbys Dollhouse
NDC: 10237-914 | Form: PASTE, DENTIFRICE
Manufacturer: Church & Dwight Co., Inc.
Category: otc | Type: HUMAN OTC DRUG LABEL
Date: 20240223

ACTIVE INGREDIENTS: SODIUM FLUORIDE 2.4 mg/1 g
INACTIVE INGREDIENTS: SORBITOL; WATER; HYDRATED SILICA; GLYCERIN; CARBOXYMETHYLCELLULOSE SODIUM, UNSPECIFIED; COCAMIDOPROPYL BETAINE; STEVIA REBAUDIUNA LEAF

Orajel™ Gabby's Dollhouse toothpaste

Drug Facts

Active Ingredient

Sodium fluoride (0.24%) (0.15% w/v fluoride ion)

Purpose

Anticavity

Use

aids in the prevention of dental decay

Warnings

Keep out of reach of children under 6 years of age. If more than used for brushing is accidentally swallowed, get medical help or contact a Poison Control Center right away.

Directions

- twist off cap and remove foil seal
- do not swallow
- supervise children as necessary until capable of using without supervision

adults and children 2 years and older | brush teeth thoroughly after meals or at least twice a day, or use as directed by a dentist or physician
children under 6 years | instruct in good brushing and rinsing habits (to minimize swallowing)
children under 2 years | ask a dentist or physician

Inactive ingredients

Sorbitol (corn), Water, Hydrated Silica (mineral), Glycerin (vegetable), Cellulose Gum (tree pulp/cotton seed), Natural Flavor, Cocamidopropyl Betaine (coconut-derived), Stevia Rebaudiana Leaf Extract (stevia). All inactive ingredients are described in the format "ingredient name (source)".

Questions or comments?

Call us at 1-800-952-5080 M-F 9am-5pm ET or visit our website at orajelkids.com

PRINCIPAL DISPLAY PANEL - 119 g Tube Label

DREAMWORKS
GABBY'S
DOLLHOUSE

STAGE
2
0-3
YEARS

Orajel™
kids

NATURALLY
SOURCED*

anti • cavity
TOOTHPASTE
fluoride

NATURAL
FRUITY
BUBBLE

OUR
COMMITMENT

CERTIFIED RENEWABLE ENERGY
Green-e®

PROUD SUPPORTER OF
Arbor Day
Foundation®

PLASTIC
TUBE

how2recycle.info

SCAN ME

NET WT 4.2 OZ (119 g)